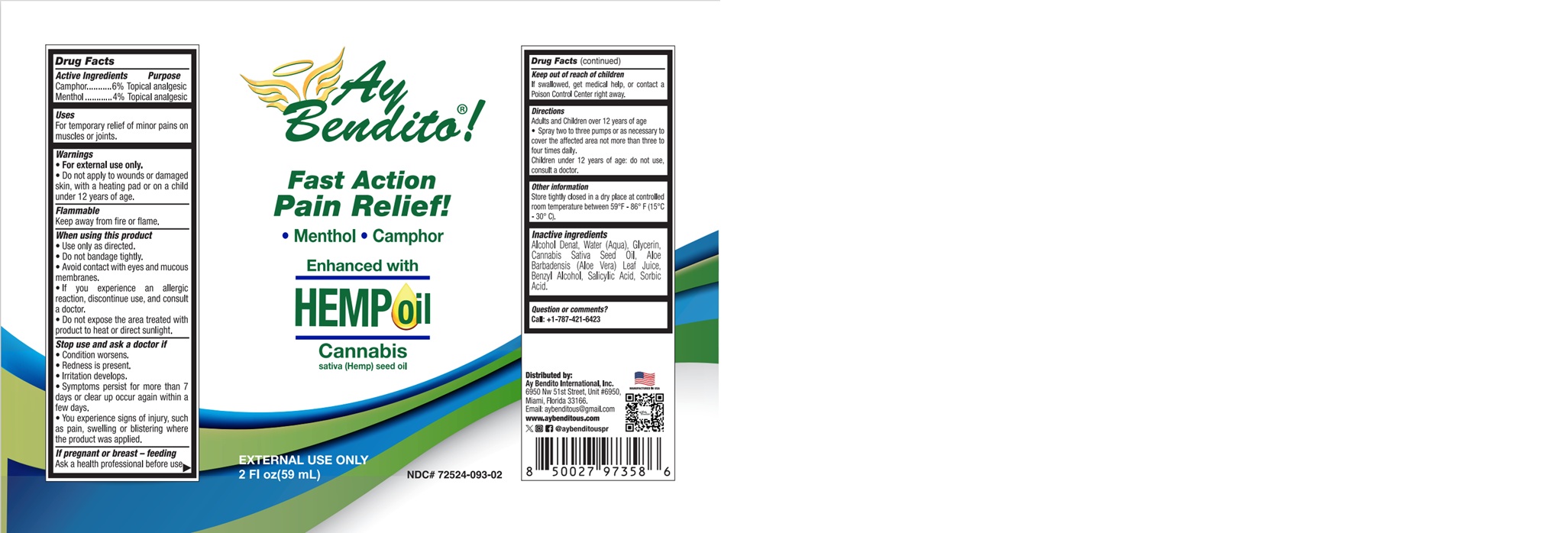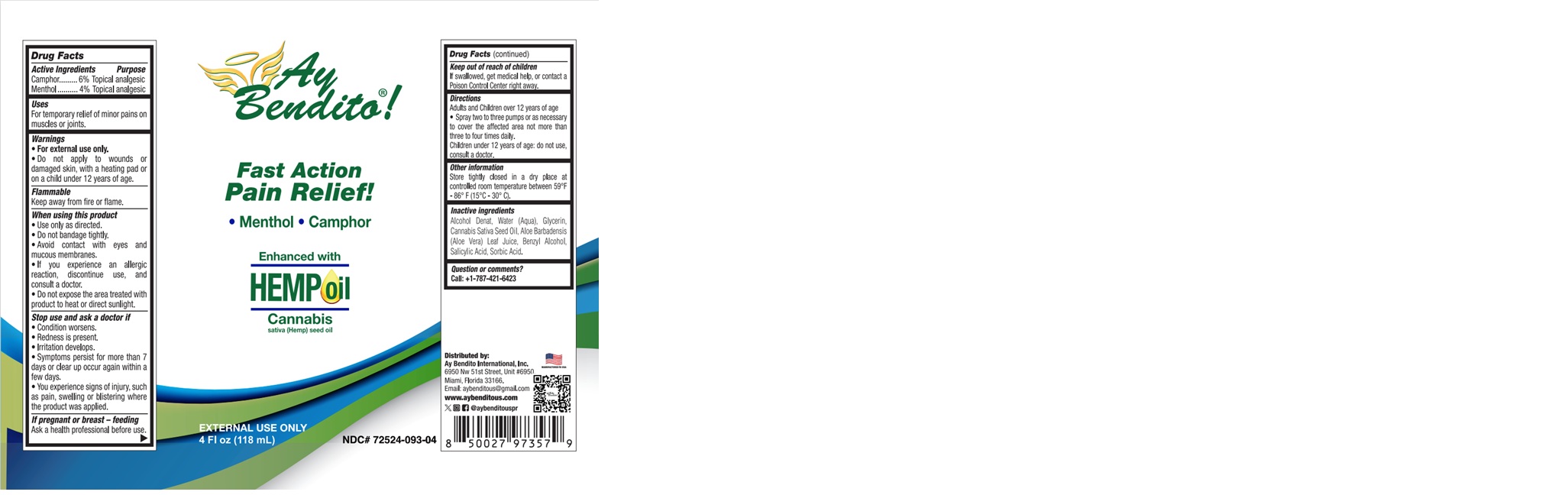 DRUG LABEL: AY BENDITO HEMP
NDC: 72524-093 | Form: SPRAY
Manufacturer: AY BENDITO INTERNATIONAL, INC
Category: otc | Type: HUMAN OTC DRUG LABEL
Date: 20251208

ACTIVE INGREDIENTS: CAMPHOR (SYNTHETIC) 5.3 g/100 mL; MENTHOL 3.6 g/100 mL
INACTIVE INGREDIENTS: WATER; SALICYLIC ACID; SORBIC ACID; BENZYL ALCOHOL; ALCOHOL; GLYCERIN; ALOE VERA LEAF JUICE; CANNABIS SATIVA SEED OIL

72524-093-02
72524-093-04

ACTIVE INGREDIENT

Camphor 6%

Menthol 4%

PURPOSE

Topical Analgesic

Use

For temporary relief of minor pains on muscles or joints.

WARNINGS

For external use only.

Do not apply to wounds or damaged skin, with a heating pad or on a child under 12 years of age.

Flammable

Keep away from fire or flame.

WHEN USING

Use only as directed.
Do not bandage tightly.
Avoid contact with eyes and mucous membranes.
If you experience an allergic reaction, discontinue use, and consult a doctor.

Do not expose the area treated with product to heat or direct sunlight.

Stop use and ask a doctor if

Condition worsens.
Redness is present.
Irritation develops.
Symptoms persist for more than 7 days or clear up occur again within a few days.

You experience signs of injury, such as pain, swelling or blistering where the product was applied.

If pregnant or breast – feeding

Ask a health professional before use.

Keep out of reach of children

If swallowed, get medical help, or contact a Poison Control Center right away.

Directions

Adults and Children over 12 years of age

Spray two to three pumps or as necessary to cover the affected area not more than three to four times daily.

Children under 12 years of age: do not use, consult a doctor.

OTHER SAFETY INFORMATION

Store tightly closed in a dry place at controlled room temperature between 59°F - 86° F (15°C - 30° C).

INACTIVE INGREDIENT

Alcohol Denat, Water (Aqua), Glycerin, Aloe Barbadensis (Aloe Vera) Leaf Juice, Cannabis Sativa (Hemp) Seed Oil, Benzyl Alcohol, Sorbic Acid, Salicylic Acid.

QUESTIONS

Call +1-787-421-6423